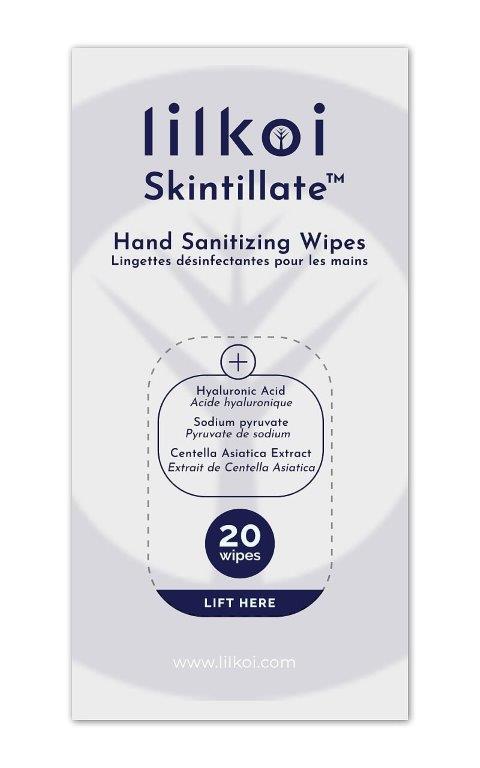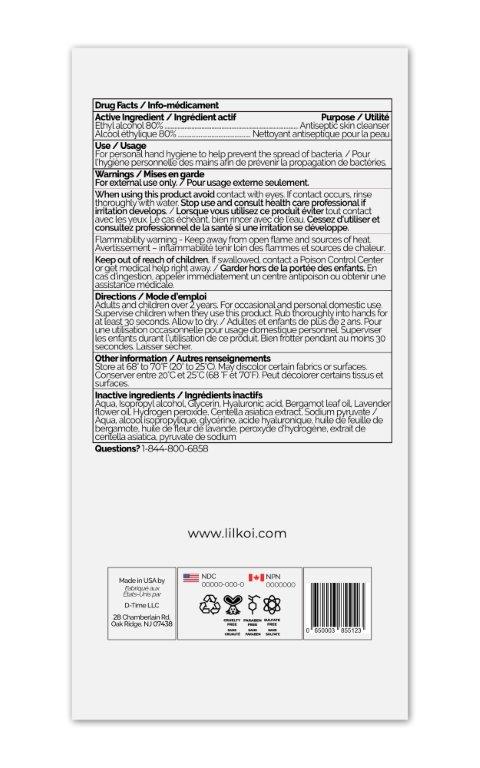 DRUG LABEL: Lilkoi Hand Sanitizing Wipes
NDC: 75306-010 | Form: CLOTH
Manufacturer: D-Time Limited Liability Company
Category: otc | Type: HUMAN OTC DRUG LABEL
Date: 20211102

ACTIVE INGREDIENTS: ALCOHOL 80 mL/100 mL
INACTIVE INGREDIENTS: WATER; ISOPROPYL ALCOHOL; GLYCERIN; HYALURONIC ACID; BERGAMOT OIL; LAVENDER OIL; HYDROGEN PEROXIDE; CENTELLA ASIATICA; SODIUM PYRUVATE

Active Ingredient

Alcohol 80% v/v.

Purpose

Antiseptic skin cleanser

Uses

For personal hand hygiene to help prevent the spread of bacteria.

Warnings

For external use only.
When using this product avoid contact with eyes. If contact occurs, rinse thoroughly with water.
Stop use and consult a healthcare professional if irritation develops.

Flammability warning: Flammable. Keep away from open flame and sources of heat.

Keep out of reach of children. If swallowed, get medical help or contact a Poison Control Center right away.

Directions

Adults and children over 2 years. For occasional and personal domestic use. Supervise children when they use this product. Rub thoroughly into hands for at least 30 seconds. Allow to dry.

Other information

- Store at 68-70 ^0F (20-25^0C)
- May discolor certain fabrics or surfaces.

Inactive ingredients

Water, Isopropyl alcohol, Glycerin, Hyaluronic Acid, Bergamot leaf oil, Lavender Flower Oil, Hydrogen Peroxide, Centella Asiatica Extract, Sodium pyruvate